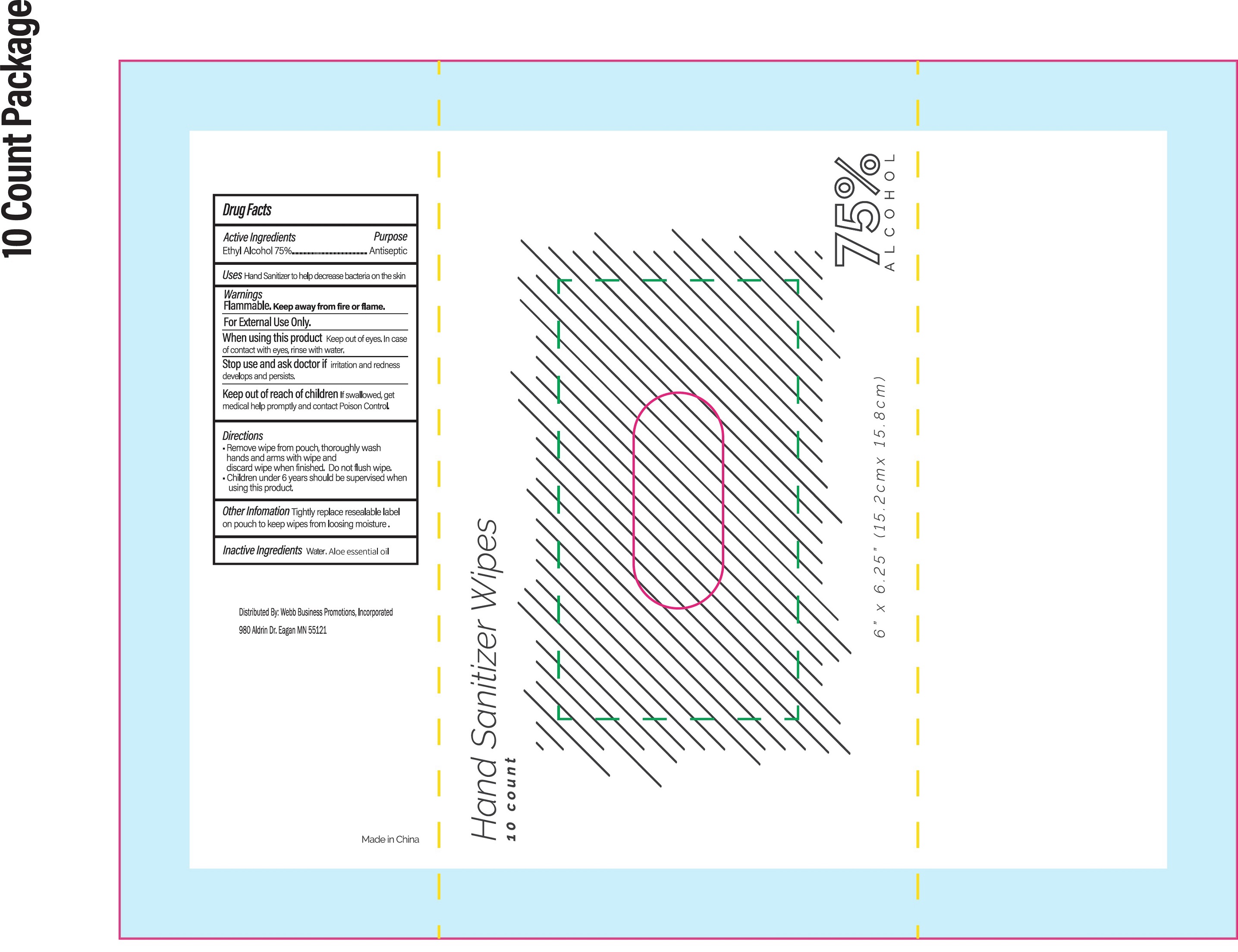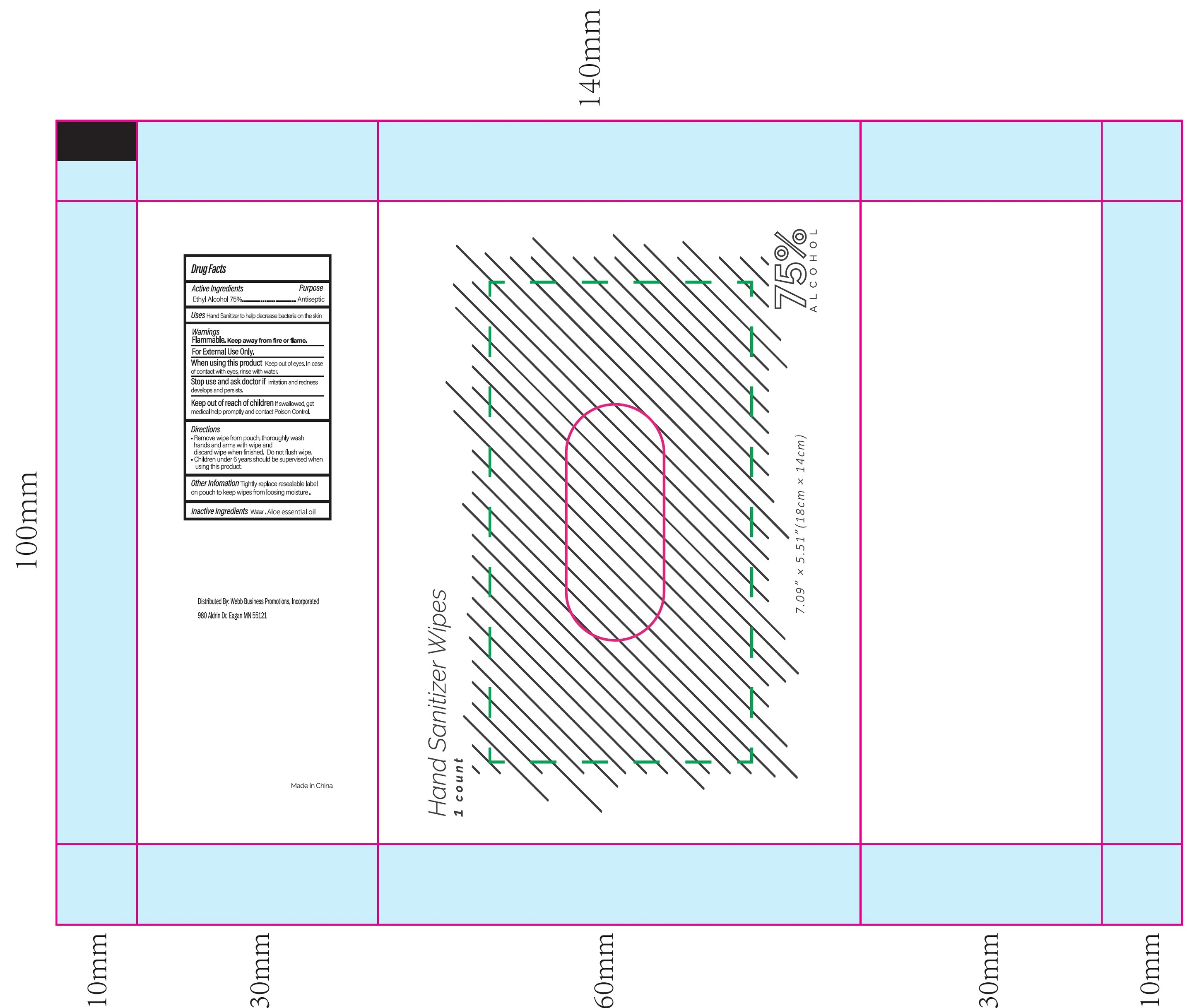 DRUG LABEL: Hand Sanitizer Wipes
NDC: 75269-011 | Form: CLOTH
Manufacturer: LINGHAI ZHANWANG BIOTECHNOLOGY CO.,LTD.
Category: otc | Type: HUMAN OTC DRUG LABEL
Date: 20231024

ACTIVE INGREDIENTS: ALCOHOL 75 mL/100 mL
INACTIVE INGREDIENTS: WATER; ALOE VERA LEAF

75269-011 Hand Sanitizer Wipes

Active Ingredients

Ethyl Alcohol 75%

Purpose

Antiseptic

Uses

Hand Sanitizer to help decrease bacteria on the skin

Warnings

Flammable. Keep away from fire or flame.

For External Use Only.

When using this product Keep out of eyes. In case of contact with eyes,rinse with water.

Stop use and ask doctor if irritation and redness develops and persists.

Keep out of reach of children If swallowed, get medical help promptly and contact Poison Control.

When using this product Keep out of eyes. In case of contact with eyes,rinse with water.

Stop use and ask doctor if irritation and redness develops and persists.

Keep out of reach of children If swallowed, get medical help promptly and contact Poison Control.

Directions

- Remove wipe from pouch, thoroughly wash hands and arms with wipe and discard wipe when finished. Do not flush wipe.
- Children under 6 years should be supervised when using this product.

Other Infomation

Tightly replace resealable label on pouch to keep wipes from loosing moisture.

Inactive Ingredients

Water, Aloe essential oil

PACKAGE LABEL

Hand Sanitizer Wipes

1 count

NDC: 75269-011-01

Hand Sanitizer Wipes

10 count

NDC: 75269-011-02